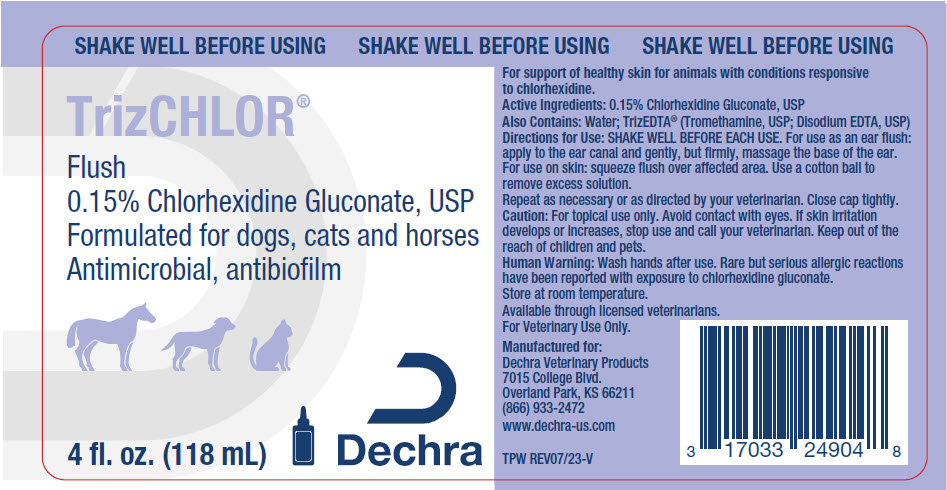 DRUG LABEL: TrizChlor Flush
NDC: 17033-249 | Form: SOLUTION
Manufacturer: Dechra Veterinary Products
Category: animal | Type: OTC ANIMAL DRUG LABEL
Date: 20240404

ACTIVE INGREDIENTS: CHLORHEXIDINE GLUCONATE 1.5 mg/1 mL

TrizChlor® Flush

VETERINARY INDICATIONS

For support of healthy skin for animals with conditions responsive to chlorhexidine.

DESCRIPTION

Active Ingredients: 0.15% Chlorhexidine Gluconate, USP

Also Contains: Water; TrizEDTA® (Tromethamine, USP; Disodium EDTA, USP)

DOSAGE AND ADMINISTRATION

Directions for Use: SHAKE WELL BEFORE EACH USE. For use as an ear flush: apply to the ear canal and gently, but firmly, massage the base of the ear. For use on skin: squeeze flush over affected area. Use a cotton ball to remove excess solution.

Repeat as necessary or as directed by your veterinarian. Close cap tightly.

SAFE HANDLING WARNING

Caution: For topical use only. Avoid contact with eyes. If skin irritation develops or increases, stop use and call your veterinarian. Keep out of the reach of children and pets.

WARNINGS

Human Warning: Wash hands after use. Rare but serious allergic reactions have been reported with exposure to chlorhexidine gluconate.

STORAGE AND HANDLING

Store at room temperature.

Available through licensed veterinarians.
Made in the USA.

Manufactured for:
Dechra Veterinary Products
7015 College Blvd.,
Overland Park, KS 66211
866.933.2472
www.dechra-us.com

TPW REV09/20

PRINCIPAL DISPLAY PANEL - 118 mL Bottle Label

SHAKE WELL BEFORE USING

TrizCHLOR®

Flush
0.15% Chlorhexidine Gluconate, USP
Formulated for dogs, cats and horses
Antimicrobial, antibiofilm

4 fl. oz. (118 mL)

Dechra